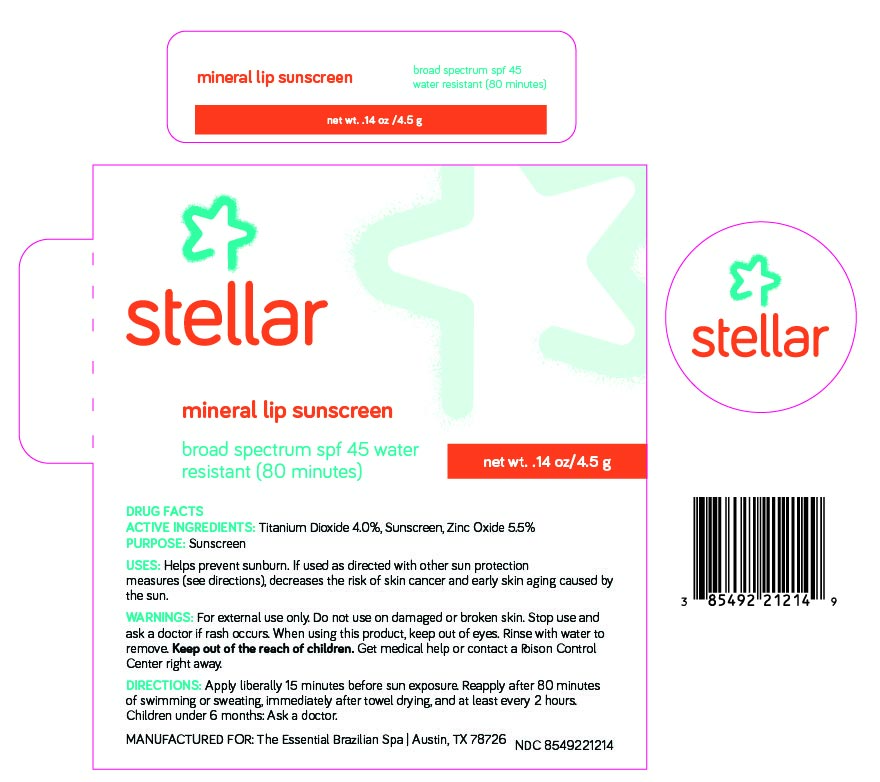 DRUG LABEL: Mineral Lip Sunscreen
NDC: 85492-212 | Form: STICK
Manufacturer: The Essential Brazilian Spa LLC
Category: otc | Type: HUMAN OTC DRUG LABEL
Date: 20251215

ACTIVE INGREDIENTS: TITANIUM DIOXIDE 40 mg/1 g; ZINC OXIDE 55 mg/1 g
INACTIVE INGREDIENTS: CITRIC ACID; HELIANTHUS ANNUUS (SUNFLOWER) SEED WAX; CETEARYL ISONONANOATE; ALUMINUM STEARATE; ASCORBIC ACID; ASCORBYL PALMITATE; CETYL DIMETHYLBUTYL ETHER; HEXYLDECANOL; HEXYLDECYL LAURATE; CI 77491; CI 77492; CI 77499; CERESIN; PEG-8; POLYGLYCERYL-3 DIISOSTEARATE; POLYHYDROXYSTEARIC ACID (2300 MW); STEARIC ACID; TOCOPHEROL; ALPHA-TOCOPHEROL ACETATE; ZINGIBER OFFICINALE (GINGER) ROOT OIL; PEG/PPG-15/15 DIMETHICONE; C12-15 ALKYL BENZOATE; DIPROPYLENE GLYCOL CAPRATE/CAPRYLATE DIESTER; LECITHIN, SOYBEAN; ALUMINUM HYDROXIDE; ETHYLHEXYL PALMITATE; ALUMINA

Active Ingredients:

Titanium Dioxide: 4%

Zinc Oxide: 5.5%

Purpose:

Sunscreen

Uses:

Helps Prevent Sunburn. If used as directed with other sun protection measures (see “Directions”), decreases the risk of skin cancer and early skin aging caused by the sun.

Warnings:

For external use only. Do not use on broken or damaged skin. Stop use and ask a doctor if rash occurs. When using this product, keep out of eyes. Rinse with water to remove. Keep out of reach of children. If swallowed, get medical help or contact a poison control center right away.

Warnings:

Keep out of reach of children

Directions:

Apply liberally 15 minutes before sun exposure. Use a water-resistant product if swimming or sweating. Reapply at least every 2 hours. Children under 6 months: Ask a doctor. Sun Protection Measures: Spending time in the sun increases your risk of skin cancer and early skin aging. To decrease this risk, regularly use a sunscreen with a Broad-Spectrum SPF value of 15 or higher and other sun protection measures including: Limit time in the sun, especially from 10 a.m. - 2 p.m. Wear long-sleeved shirts, pants, hats and sunglasses.

Inactive Ingredients:

Alumina, Aluminum Hydroxide, Aluminum Stearate, Asorbic Acid, Ascorbyl Palmitate, C12-15Alkyl Benzoate, Cetearyl Isononanoate, Cetyl PEG/PPG-15/15 Butyl Ether Dimethicone, Citric Acid, Dipropylene Glycol Dicaprylate-Caprate, Ethylhexyl Palmitate, Flavor, Helianthus annuus (Sunflower) Seed Wax, Hexyldecanol, Hexyldecyl Laurate, Iron Oxide, Lecithin, Ozokerite, PEG-8, Polyglyceryl-3 Diisostearate, Polyhydroxystearic Acid, Stearic Acid, Tocopherol, Tocopheryl Acetate, Zingiber Officinale (Ginger) Root Oil